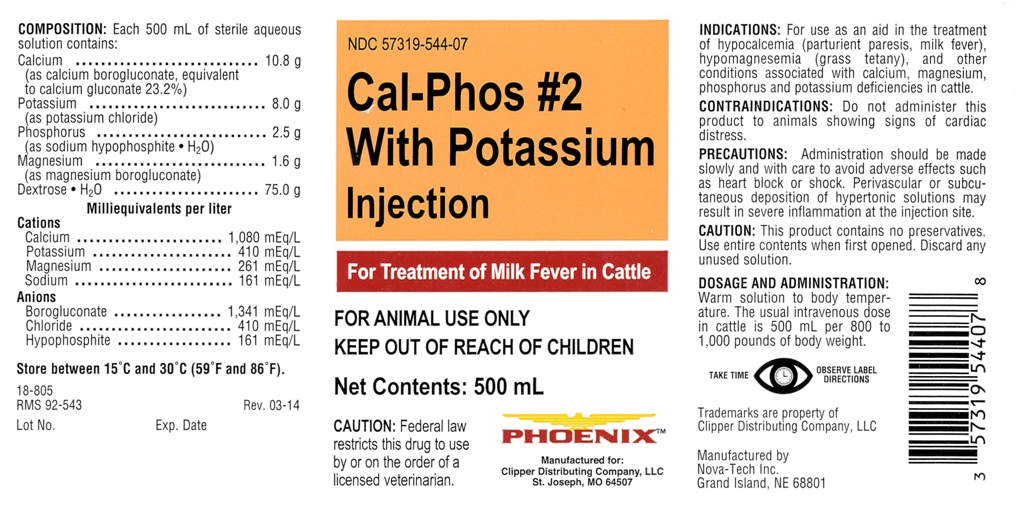 DRUG LABEL: Cal-Phos 2 With Potassium
NDC: 57319-544 | Form: INJECTION, SOLUTION
Manufacturer: Clipper
Category: animal | Type: PRESCRIPTION ANIMAL DRUG LABEL
Date: 20150901

ACTIVE INGREDIENTS: Dextrose monohydrate 75.0 g/500 mL; Potassium Chloride 8.0 g/500 mL; Calcium Gluconate Monohydrate 10.8 g/500 mL; Phosphorus 2.5 g/500 mL; Magnesium Gluconate 1.6 g/500 mL

Cal-Phos #2 With Potassium Injection

COMPOSITION:

Each 500 mL of sterile aqueous
solution contains:
Calcium ......................... 10.8 g
(as calcium borogluconate, equivalent
to calcium gluconate 23.2%)
Potassium ....................... 8.0 g
(as potassium chloride)
Phosphorus ..................... 2.5 g
(as sodium hypophosphite.H2O)
Magnesium ..................... 1.6 g
(as magnesium borogluconate)
Dextrose.H2O ................ 75.0 g

Milliequivalents per liter

Cations
Calcium .................. 1,080 mEq/L
Potassium ................. 410 mEq/L
Magnesium ............... 261 mEq/L
Sodium .................... 161 mEq/L

Anions
Borogluconate ......... 1,341 mEq/L
Chloride .................... 410 mEq/L
Hypophosphite ........... 161 mEq/L

INDICATIONS:

For use as an aid in the treatment
of hypocalcemia (parturient paresis, milk fever),
hypomagnesemia (grass tetany), and other
conditions associated with calcium, magnesium,
phosphorus and potassium deficiencies in cattle.

CONTRAINDICATIONS:

Do not administer this
product to animals showing signs of cardiac
distress.

PRECAUTIONS:

Administration should be made
slowly and with care to avoid adverse effects such
as heart block or shock. Perivascular or subcu-
taneous deposition of hypertonic solutions may
result in severe inflammation at the injection site.

CAUTION:

This product contains no preservatives.
Use entire contents when first opened. Discard any
unused solution.

DOSAGE AND ADMINISTRATION:

Warm solution to body temper-
ature. The usual intravenous dose
in cattle is 500 mL per 800 to
1,000 pounds of body weight.

STORAGE AND HANDLING

Store between 15 degrees C and 30 degrees C (59 degrees F and 86 degrees F).

VETERINARY INDICATIONS

FOR ANIMAL USE ONLY

CAUTION:

Federal law
restricts this drug to use
by or on the order of a
licensed veterinarian.

KEEP OUT OF REACH OF CHILDREN

TAKE TIME OBSERVE LABEL DIRECTIONS

INFORMATION FOR OWNERS/CAREGIVERS

18-805
RMS 92-543 Rev. 03-14

Lot No. Exp. Date

For Treatment of Milk Fever in Cattle

Net Contents: 500 mL

Manufactured for:
Clipper Distributing Company, LLC
St. Joseph, MO 64507

Trademarks are property of
Clipper Distributing Company, LLC

Manufactured by
Nova-Tech Inc.
Grand Island, NE 68801